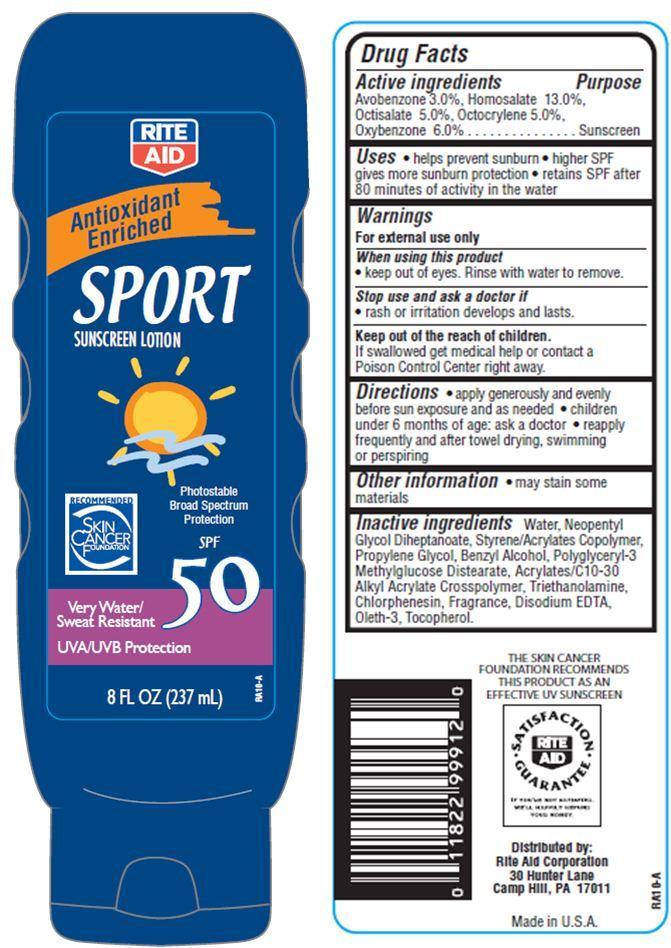 DRUG LABEL: Rite Aid Sport SunscreenSPF 50
          
NDC: 11822-9001 | Form: LOTION
Manufacturer: RITE AID CORPORATION
Category: otc | Type: HUMAN OTC DRUG LABEL
Date: 20121121

ACTIVE INGREDIENTS: AVOBENZONE 3 g/100 g; HOMOSALATE 13 g/100 g; OCTISALATE 5 g/100 g; OCTOCRYLENE 5 g/100 g; OXYBENZONE 6 g/100 g
INACTIVE INGREDIENTS: WATER; NEOPENTYL GLYCOL DIHEPTANOATE; TROLAMINE; BENZYL ALCOHOL; CHLORPHENESIN; OLETH-3; TOCOPHEROL; EDETATE DISODIUM; PROPYLENE GLYCOL

Drug Facts

Active Ingredients

Avobenzone 3.0 %

Homosalate 13.0%

Octisalate 5.0%

Octocrylene 5.0%

Oxybenzone 6.0%

Purpose

Sunscreen

Uses

- helps prevent sunburn
- higher SPF gives more sunburn protection
- retains SPF after 80 minutes of activity in the water

Warnings

For external use only

When using this product

- keep out of eyes. Rinse with water to remove.

Stop use and ask a doctor if

- rash or irritation develops and lasts

keep out of reach of children

If swallowed, get medical help or contact a Poison Control Center right away.

Directions

- apply generously and evenly before sun exposure and as needed
- children under 6 months of age:ask a doctor
- reapply frequently and after towel drying, swimming or perspiring.

Other Information

- may stain some materials.

Inactive Ingredients

Water, Neopentyl Glycol Diheptanoate, Styrene/Acrylates Copolymer, Propylene Glycol, Polyglyceryl-3 Methylglucose Distearate, Benzyl Alcohol, Acrylates/C10-30 Alkyl Acrylate Crosspolymer, Triethanolamine, Disodium EDTA, Oleth-3, Tocopherol, Chlorphenesin, Fragrance.

Principal Display Panel

RITE
AID
Antioxidant
Enriched
SPORT
SUNSCREEN LOTION
Photostable
Broad Spectrum
Protection
SPF
50
RECOMMENDED
SKIN CANCER
FOUNDATION
Very Water/
Sweat Resistant
UVA/UVB Protection
8 FL OZ (237 mL)